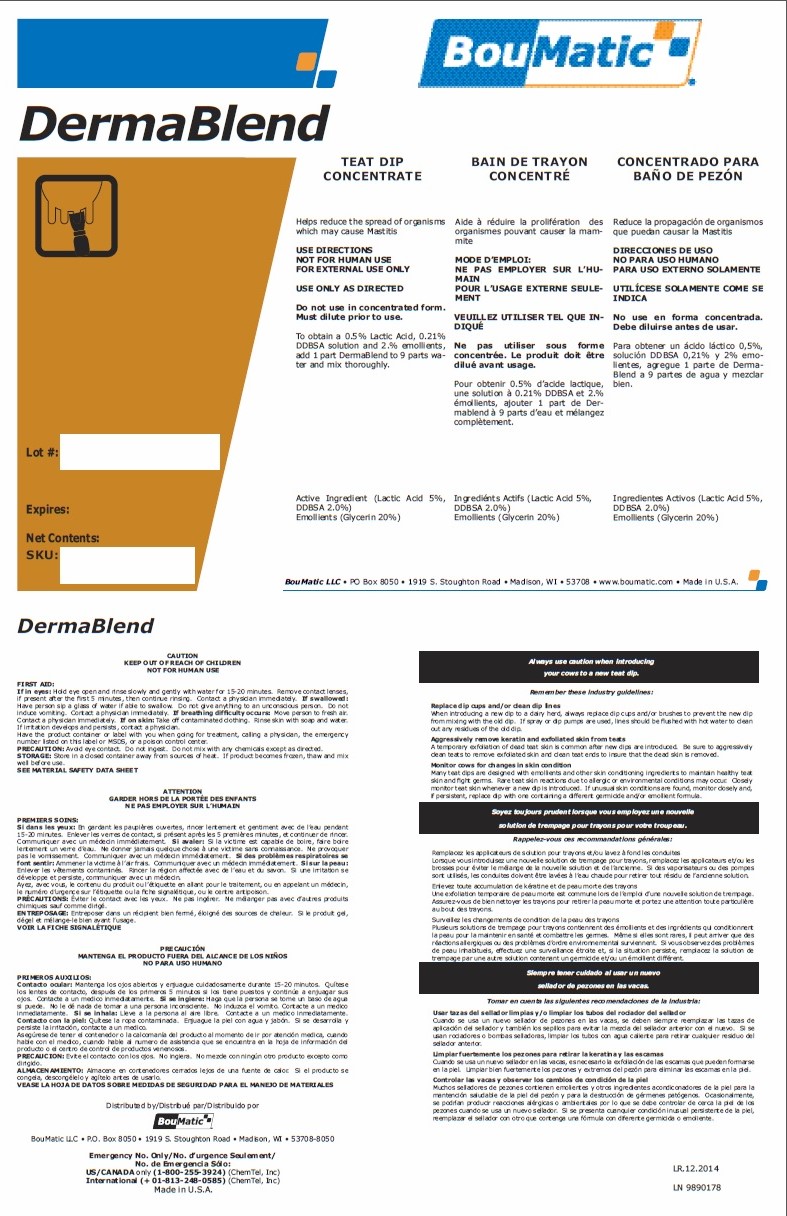 DRUG LABEL: DERMABLEND
NDC: 48106-1316 | Form: CONCENTRATE
Manufacturer: BouMatic, LLC
Category: animal | Type: OTC ANIMAL DRUG LABEL
Date: 20150101

ACTIVE INGREDIENTS: LACTIC ACID 50 g/1 L; DODECYLBENZENESULFONIC ACID 20 g/1 L

DERMABLEND

INDICATIONS AND USAGE

Enter section text here

TEAT DIP CONCENTRATE

Helps reduce the spread of organisms which may cause Mastitis

USE DIRECTIONS

NOT FOR HUMAN USE

FOR EXTERNAL USE ONLY

USE ONLY AS DIRECTED

Do not use in concentrated form.
Must dilute prior to use.

To obtain a 0.5% Lactic Acid, 0.21%
DDBSA solution and 2.% emollients,
add 1 part DermaBlend to 9 parts water
and mix thoroughly.

Active Ingredient (Lactic Acid 5%,
DDBSA 2.0%)
Emollients (Glycerin 20%)

PRECAUTIONS

Enter section text here

CAUTION

KEEP OUT OF REACH OF CHILDREN

NOT FOR HUMAN USE

FIRST AID:
If in eyes: Hold eye open and rinse slowly and gently with water for 15-20 minutes. Remove contact lenses,
if present after the first 5 minutes, then continue rinsing. Contact a physician immediately.

If swallowed: Have person sip a glass of water if able to swallow. Do not give anything to an unconscious person. Do not
induce vomiting. Contact a physician immediately.

If breathing difficulty occurs: Move person to fresh air. Contact a physician immediately.

If on skin: Take off contaminated clothing. Rinse skin with soap and water. If irritation develops and persists, contact a physician.

Have the product container or label with you when going for treatment, calling a physician, the emergency
number listed on this label or MSDS, or a poison control center.

PRECAUTION: Avoid eye contact. Do not ingest. Do not mix with any chemicals except as directed.

STORAGE: Store in a closed container away from sources of heat. If product becomes frozen, thaw and mix
well before use.

SEE MATERIAL SAFETY DATA SHEET

PACKAGE LABEL

Enter section text here